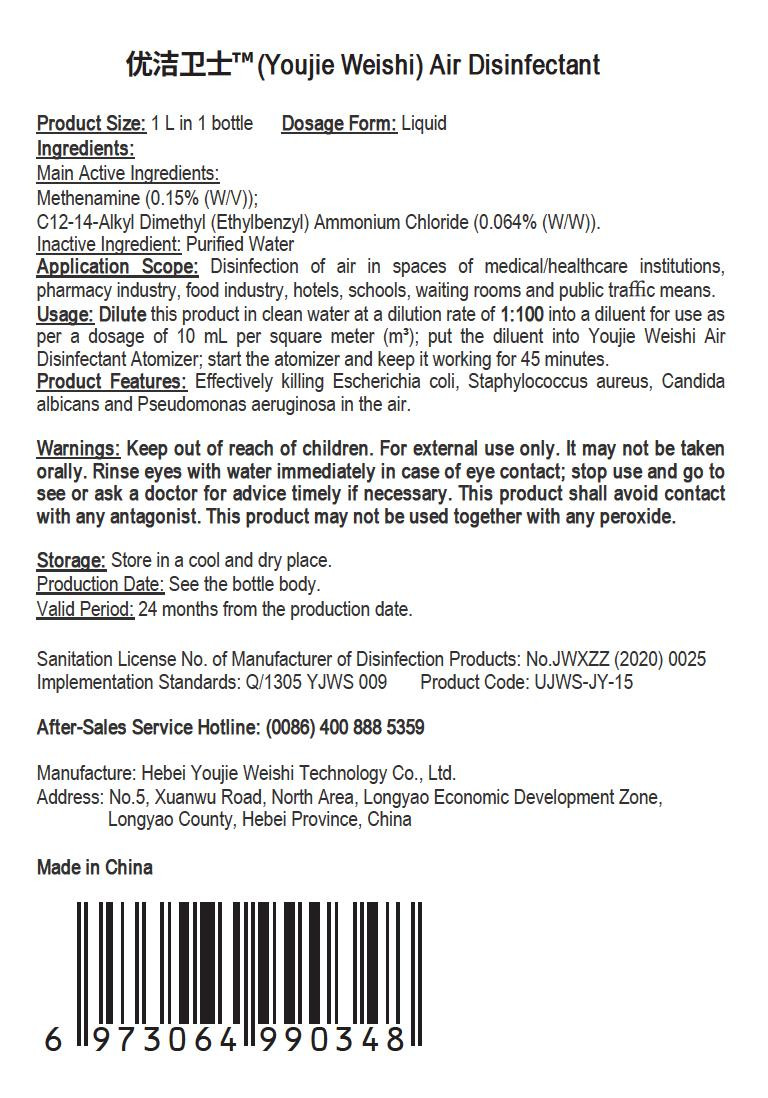 DRUG LABEL: Youjie Weishi Air Disinfectant
NDC: 55455-005 | Form: LIQUID
Manufacturer: Hebei Youjie Weishi Technology Co., Ltd.
Category: otc | Type: HUMAN OTC DRUG LABEL
Date: 20200507

ACTIVE INGREDIENTS: MYRISTALKONIUM CHLORIDE 0.64 g/1000 mL; METHENAMINE 1.5 g/1000 mL
INACTIVE INGREDIENTS: WATER

PURPOSE

Disinfection
Sterilization
No Rinseing

INACTIVE INGREDIENT

water

DOSAGE AND ADMINISTRATION

Store in a cool and dry place.

ACTIVE INGREDIENT

Methenamine

C12-14-Alkyldimethyl(ethylbenzyl)ammonium chloride

keep out of reach of children

INDICATIONS AND USAGE

Dilute this product in clean water at a dilution rate of 1:100 into a diluent for use as per a dosage of 10 mL per square meter (m); put the diluent into Youjie Weishi Air Disinfectant Atomizer; start the atomizer and keep it working for 45 minutes.

Keep out of reach of children. For external use only. It may not be taken orally. Rinse eyes with water immediately in case of eye contact; stop use and go to see or ask a doctor for advice timely if necessary. This product shall avoid contact with any antagonist. This product may not be used together with any peroxide.